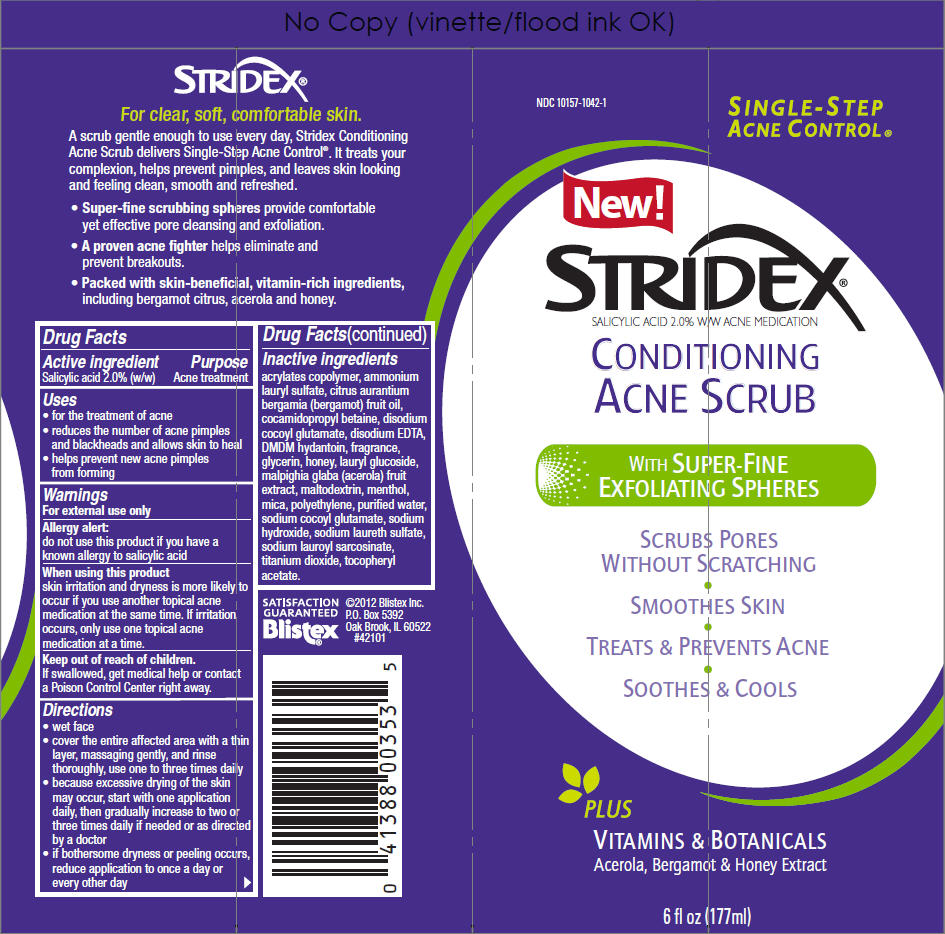 DRUG LABEL: Stridex Conditioning Acne Scrub
NDC: 10157-1042 | Form: GEL
Manufacturer: Blistex Inc
Category: otc | Type: HUMAN OTC DRUG LABEL
Date: 20121115

ACTIVE INGREDIENTS: Salicylic Acid 2 g/100 mL
INACTIVE INGREDIENTS: ammonium lauryl sulfate; bergamot oil; cocamidopropyl betaine; disodium cocoyl glutamate; Edetate Disodium; DMDM hydantoin; glycerin; honey; lauryl glucoside; malpighia glabra fruit; maltodextrin; menthol; mica; high density polyethylene; water; sodium cocoyl glutamate; sodium hydroxide; sodium laureth-3 sulfate; sodium lauroyl sarcosinate; titanium dioxide; .alpha.-tocopherol acetate

Stridex® Conditioning Acne Scrub

Drug Facts

Active ingredient

Salicylic acid 2.0% (w/w)

Purpose

Acne treatment

Uses

- for the treatment of acne
- reduces the number of acne pimples and blackheads and allows skin to heal
- helps prevent new acne pimples from forming

Warnings

For external use only

Allergy alert

do not use this product if you have a known allergy to salicylic acid

When using this product

skin irritation and dryness is more likely to occur if you use another topical acne medication at the same time. If irritation occurs, only use one topical acne medication at a time.

Keep out of reach of children.

If swallowed, get medical help or contact a Poison Control Center right away.

Directions

- wet face
- cover the entire affected area with a thin layer, massaging gently, and rinse thoroughly, use one to three times daily
- because excessive drying of the skin may occur, start with one application daily, then gradually increase to two or three times daily if needed or as directed by a doctor
- if bothersome dryness or peeling occurs, reduce application to once a day or every other day

Inactive ingredients

acrylates copolymer, ammonium lauryl sulfate, citrus aurantium bergamia (bergamot) fruit oil, cocamidopropyl betaine, disodium cocoyl glutamate, disodium EDTA, DMDM hydantoin, fragrance, glycerin, honey, lauryl glucoside, malpighia glaba (acerola) fruit extract, maltodextrin, menthol, mica, polyethylene, purified water, sodium cocoyl glutamate, sodium hydroxide, sodium laureth sulfate, sodium lauroyl sarcosinate, titanium dioxide, tocopheryl acetate.

PRINCIPAL DISPLAY PANEL - 177mL Tube Label

NDC 10157-1042-1

SINGLE-STEP
ACNE CONTROL®

New!

STRIDEX®
SALICYLIC ACID 2.0% W/W ACNE MEDICATION

CONDITIONING
ACNE SCRUB

WITH SUPER-FINE
EXFOLIATING SPHERES

SCRUBS PORES
WITHOUT SCRATCHING

SMOOTHES SKIN

TREATS & PREVENTS ACNE

SOOTHES & COOLS

PLUS

VITAMINS & BOTANICALS
Acerola, Bergamot & Honey Extract

6 fl oz (177ml)